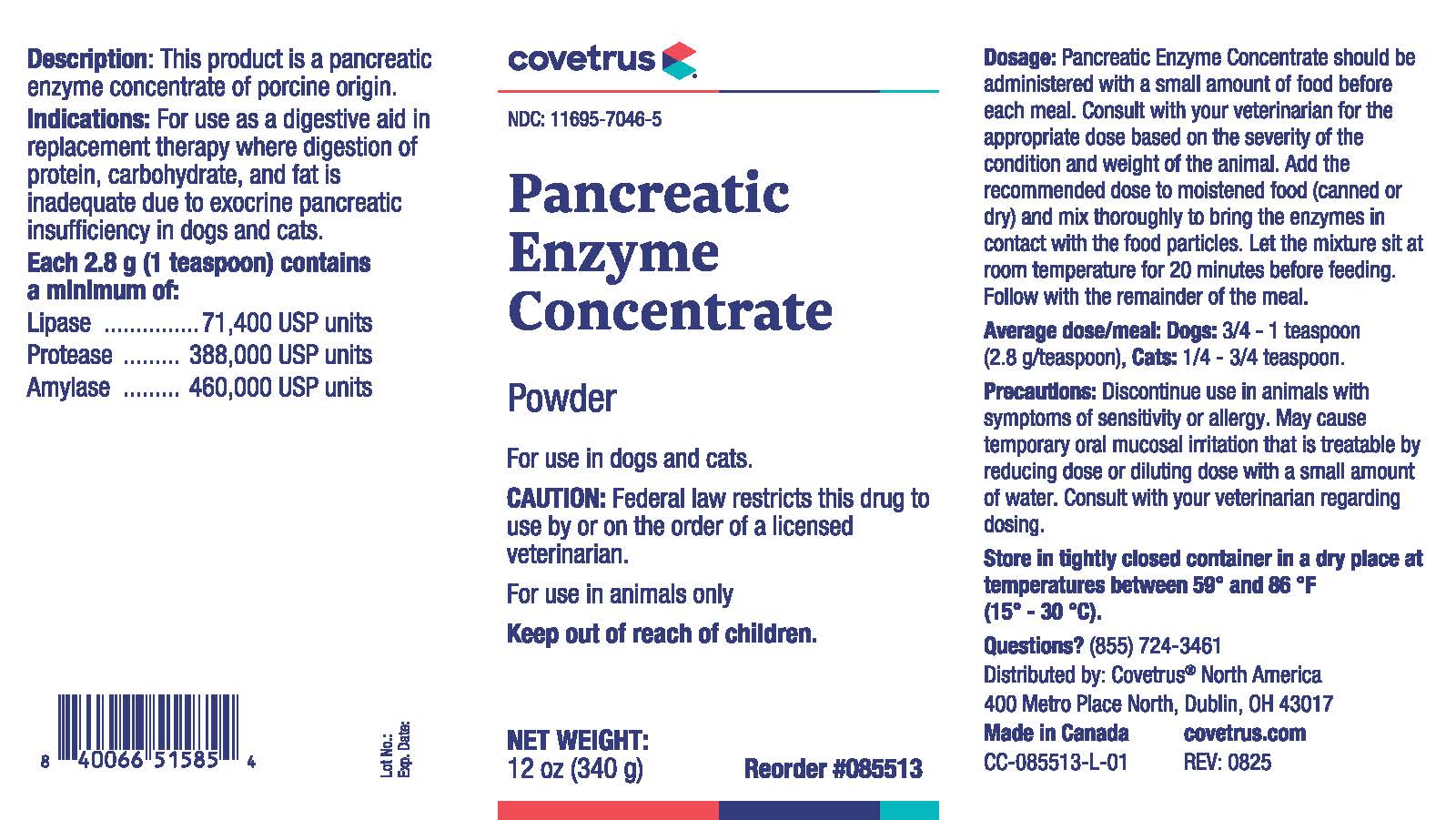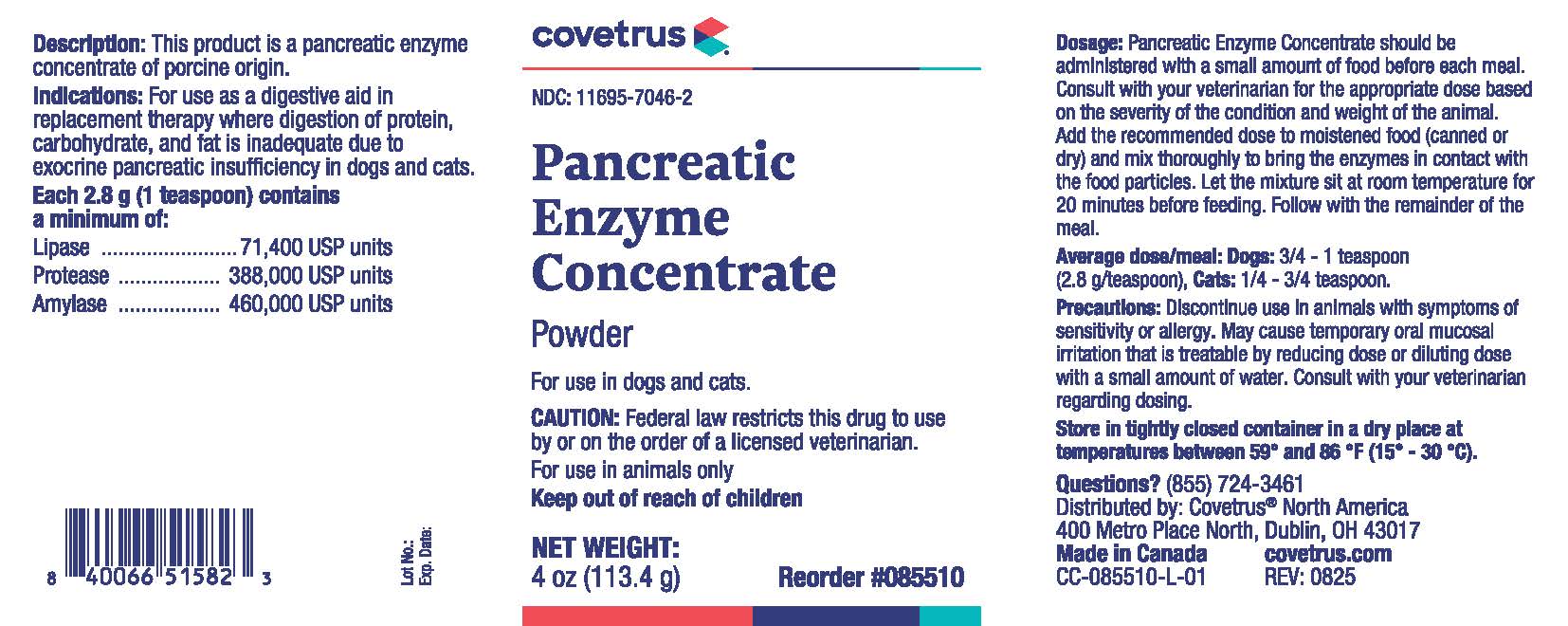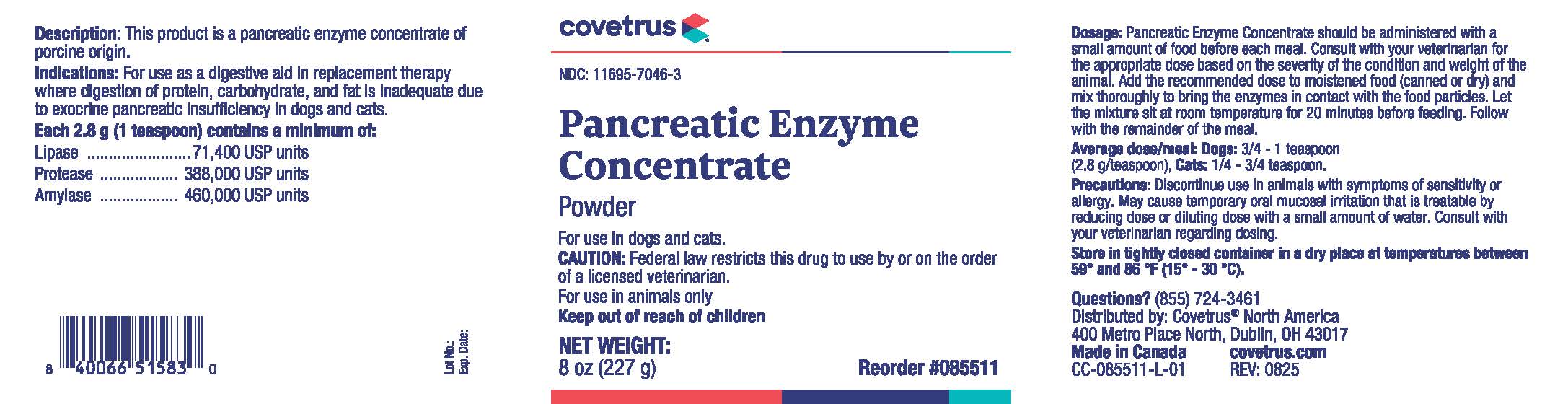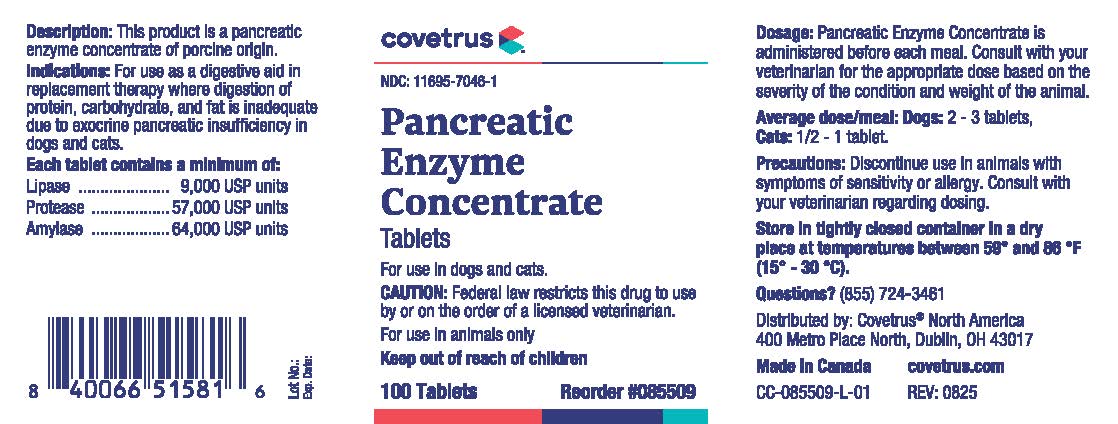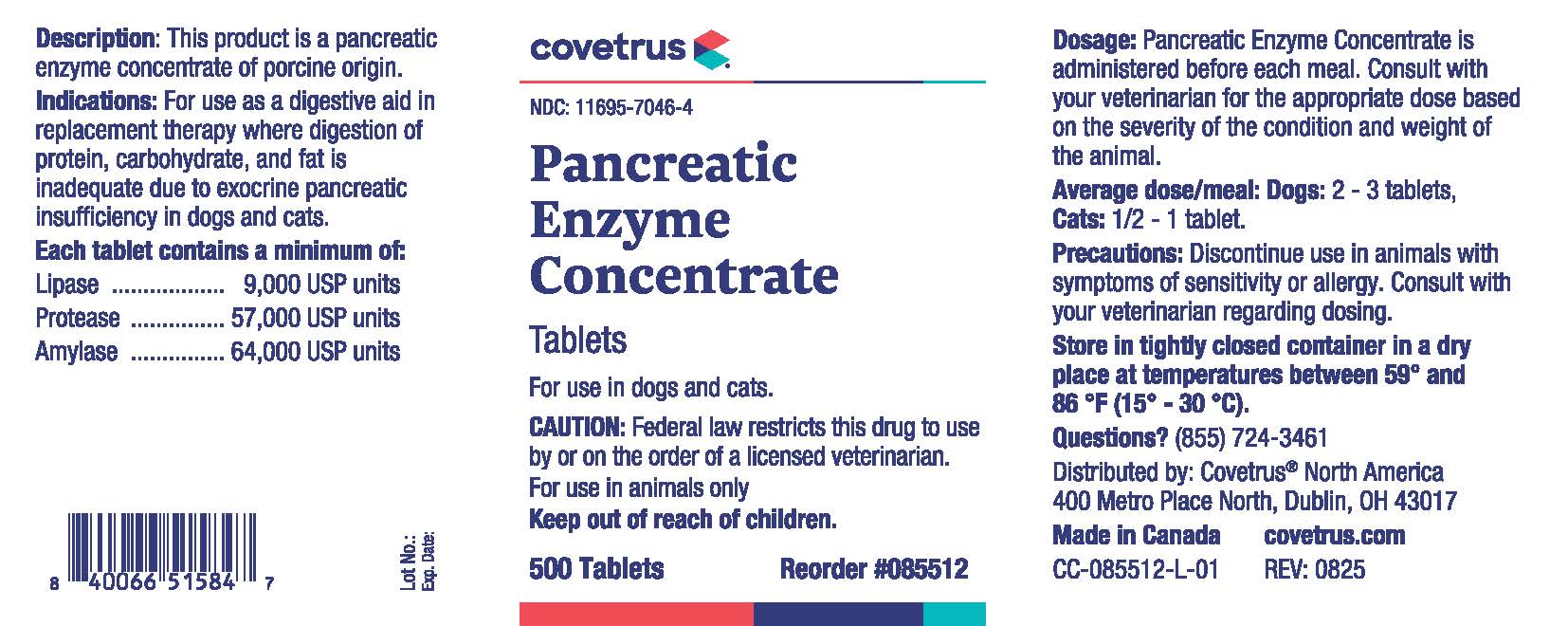 DRUG LABEL: Pancreatic Enzyme Concentrate
NDC: 11695-7046 | Form: TABLET
Manufacturer: Covetrus North America
Category: animal | Type: OTC ANIMAL DRUG LABEL
Date: 20260211

ACTIVE INGREDIENTS: PANCRELIPASE LIPASE 9000 U/1 1; PANCRELIPASE PROTEASE 57000 U/1 1; PANCRELIPASE AMYLASE 64000 U/1 1

Pancreatic Enzyme Concentrate

For use in dogs and cats.

CAUTION:

Federal law restricts this drug to use by or on the order of a licensed veterinarian.

For use in animals only

Keep out of reach of children

Description:

This product is a pancreatic enzyme concentrate of porcine origin.

Indications:

For use as a digestive aid in replacement therapy where digestion of protein, carbohydrate, and fat is inadequate due to exocrine pancreatic insufficiency in dogs and cats.

Each tablet contains a minimum of:

Lipase 9,000 USP units

Protease 57,000 USP units

Amylase 64,000 USP units

Each 2.8g (1 teaspoon) of powder contains a minimum of:

Lipase 71,400 USP units

Protease 388,000 USP units

Amylase 460,000 USP units

Dosage:

Tablets

Pancreatic Enzyme Concentrate is administered before each meal. Consult with your veterinarian for the appropriate dose based on the severity of the condition and weight of the animal.

Average dose/meal:

Dogs: 2 - 3 tablets

Cats: 1/2 - 1 tablet

Powder

Pancreatic Enzyme Concentrate should be administered with a small amount of food before each meal. Consult your veterinarian for the appropriate dose based on the severity of the condition and weight of the animal. Add the recommended dose to moistened food (canned or dry) and mix thoroughly to bring the enzymes in contact with the food particles. Let the mixture sit at room temperature for 20 minutes before feeding. Follow with the remainder of the meal.

Average dose/meal:

Dogs: 3/4 - 1 teaspoon (2.8g/teaspoon)

Cats: 1/4 - 3/4 teaspoon

Precautions:

Tablet

Discontinue use in animals with symptoms of sensitivity or allergy. Consult with your veterinarian regarding dosing.

Powder

Discontinue use in animals with symptoms of sensitivity or allergy. May cause temporary oral mucosal irritation that is treatable by reducing dose or diluting dose with a small amount of water. Consult your veterinarian regarding dosing.

PACKAGE LABEL

Pancreatic Enzyme Concentrate Tablets - 100 Count

Pancreatic Enzyme Concentrate Tablets - 500 Count

Pancreatic Enzyme Concentrate Powder - 4 Ounce Jar

Pancreatic Enzyme Concentrate Powder - 8 Ounce Jar

Pancreatic Enzyme Concentrate Powder - 12 Ounce Jar